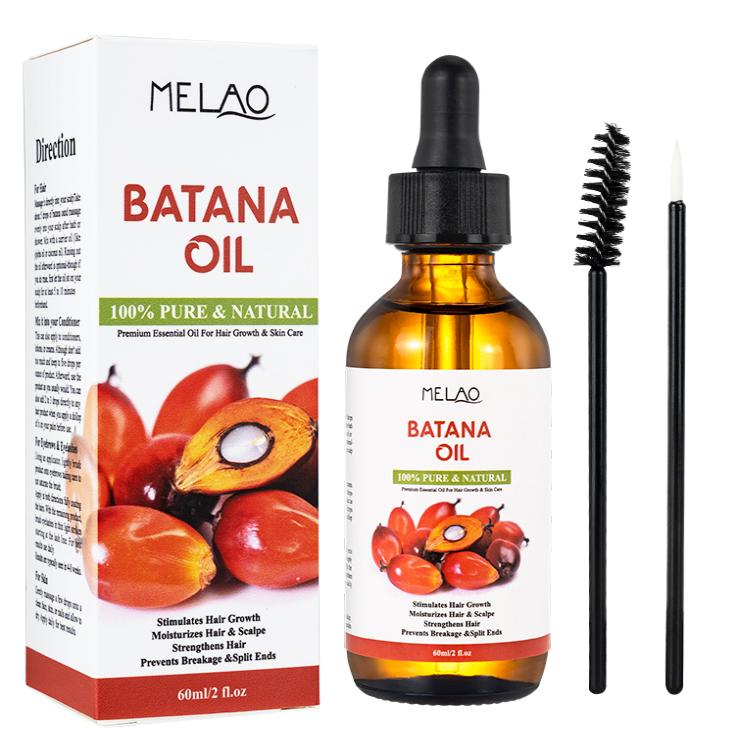 DRUG LABEL: MELAO BATANA Oil
NDC: 83566-593 | Form: LIQUID
Manufacturer: Guangzhou Yilong Cosmetics Co., Ltd
Category: otc | Type: HUMAN OTC DRUG LABEL
Date: 20240827

ACTIVE INGREDIENTS: ABIES ALBA LEAF OIL 100 g/100 g
INACTIVE INGREDIENTS: ABIES ALBA WOOD OIL

MELAO BATANA OIL

Active ingredients

Cera Alba 100%

Inactive ingredients

NONE

-Purpose

-Moisture

Uses

Step 1: Clean and thoroughly dry your hair.

Step 2: Rotate the bottle cap to open the product.

Step 3: Gently apply to the surface of the hair.

Warning

For external use only.

.Stop use and ask a doctor if

rash occurs.

Stop use and ask a doctor if

rash occurs.

Do not use

on damaged or broken skin.

When using this product

keep out of eyes. Rinse withwater to remove.

DOSAGE & ADMINISTRATION

Squeeze out an appropriate amount of product and spread evenly on skin.

keep out of children